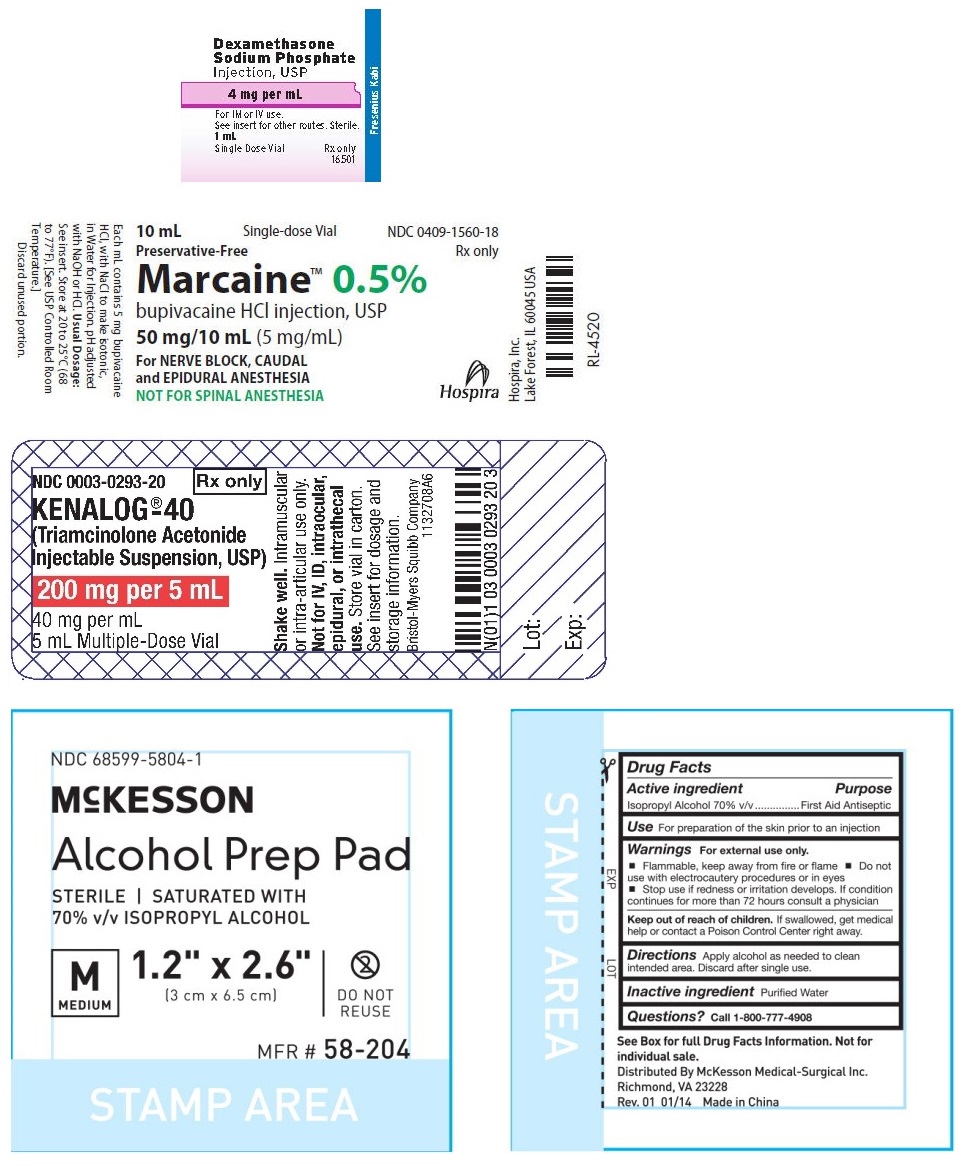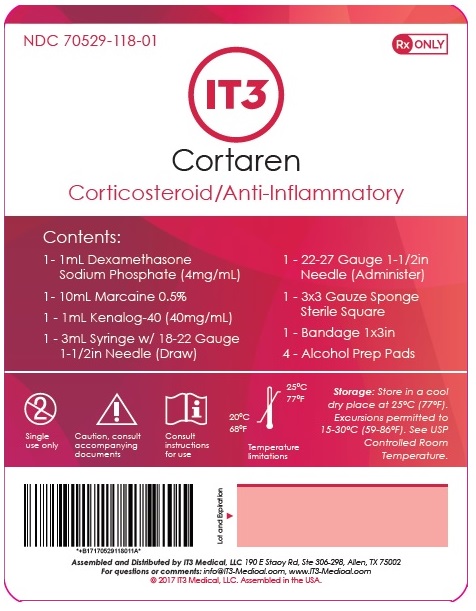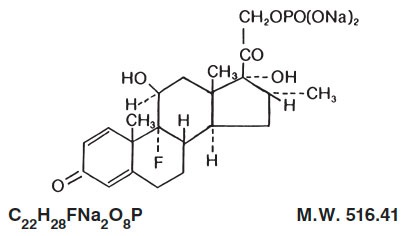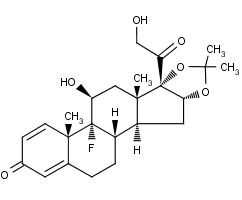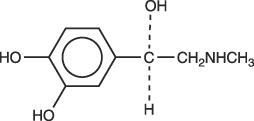 DRUG LABEL: Cortaren Corticosteroid/Anti-Inflammatory System
NDC: 70529-118 | Form: KIT | Route: INTRAMUSCULAR
Manufacturer: IT3 Medical LLC
Category: prescription | Type: HUMAN PRESCRIPTION DRUG LABEL
Date: 20220224

ACTIVE INGREDIENTS: DEXAMETHASONE SODIUM PHOSPHATE 4 mg/1 mL; BUPIVACAINE HYDROCHLORIDE 5 mg/1 mL; TRIAMCINOLONE ACETONIDE 40 mg/1 mL; ISOPROPYL ALCOHOL 0.7 mL/1 mL
INACTIVE INGREDIENTS: SODIUM CITRATE, UNSPECIFIED FORM 11 mg/1 mL; SODIUM SULFITE 1 mg/1 mL; BENZYL ALCOHOL 10 mg/1 mL; SODIUM HYDROXIDE; CITRIC ACID MONOHYDRATE; SODIUM CHLORIDE; SODIUM HYDROXIDE; HYDROCHLORIC ACID; WATER; SODIUM CHLORIDE; BENZYL ALCOHOL; POLYSORBATE 80; SODIUM HYDROXIDE; HYDROCHLORIC ACID; NITROGEN; CARBOXYMETHYLCELLULOSE SODIUM, UNSPECIFIED FORM; WATER

Cortaren Corticosteroid/Anti-Inflammatory System

Dexamethasone Sodium Phosphate Injection, USP

Rx only

DESCRIPTION:

Dexamethasone sodium phosphate is a water-soluble inorganic ester of dexamethasone. It occurs as a white or slightly yellow crystalline powder, is odorless or has a slight odor of alcohol, is exceedingly hygroscopic and is freely soluble in water.

Dexamethasone sodium phosphate is an adrenocortical steroid anti-inflammatory drug.

Chemically, dexamethasone sodium phosphate is 9-Fluoro-11ß,17,21-trihydroxy-16α-methylpregna-1, 4-diene-3,20-dione 21-(dihydrogen phosphate) disodium salt and has the following structural formula:

Dexamethasone Sodium Phosphate Injection, USP is a sterile solution of dexamethasone sodium phosphate in water for injection for intravenous (IV), intramuscular (IM), intra-articular, soft-tissue or intralesional use.

Each mL contains dexamethasone sodium phosphate equivalent to dexamethasone phosphate 4 mg or dexamethasone 3.33 mg; benzyl alcohol 10 mg added as preservative; sodium citrate dihydrate 11 mg; sodium sulfite 1 mg as an antioxidant; Water for Injection q.s. Citric acid and/or sodium hydroxide may have been added for pH adjustment (7.0 to 8.5). Air in the container is displaced by nitrogen.

CLINICAL PHARMACOLOGY:

Dexamethasone sodium phosphate has a rapid onset but short duration of action when compared with less soluble preparations. Because of this, it is suitable for the treatment of acute disorders responsive to adrenocortical steroid therapy.

Naturally occurring glucocorticoids (hydrocortisone and cortisone), which also have salt-retaining properties, are used as replacement therapy in adrenocortical deficiency states. Their synthetic analogs, including dexamethasone, are primarily used for their potent anti-inflammatory effects in disorders of many organ systems.

Glucocorticoids cause profound and varied metabolic effects. In addition, they modify the body’s immune responses to diverse stimuli.

At equipotent anti-inflammatory doses, dexamethasone almost completely lacks the sodium-retaining property of hydrocortisone and closely related derivatives of hydrocortisone.

INDICATIONS AND USAGE:

Intravenous or Intramuscular Injection

When oral therapy is not feasible and the strength, dosage form, and route of administration of the drug reasonably lend the preparation to the treatment of the condition, those products labeled for intravenous or intramuscular use are indicated as follows:

• Endocrine Disorders

Primary or secondary adrenocortical insufficiency (hydrocortisone or cortisone is the drug of choice; synthetic analogs may be used in conjunction with mineralocorticoids where applicable; in infancy, mineralocorticoid supplementation is of particular importance)

Acute adrenocortical insufficiency (hydrocortisone or cortisone is the drug of choice; mineralocorticoid supplementation may be necessary, particularly when synthetic analogs are used)

Preoperatively, and in the event of serious trauma or illness, in patients with known adrenal insufficiency or when adrenocortical reserve is doubtful

Shock unresponsive to conventional therapy if adrenocortical insufficiency exists or is suspected

Congenital adrenal hyperplasia

Nonsuppurative thyroiditis

Hypercalcemia associated with cancer

• Rheumatic Disorders

As adjunctive therapy for short-term administration (to tide the patient over an acute episode or exacerbation) in:

Post-traumatic osteoarthritis

Synovitis of osteoarthritis

Rheumatoid arthritis, including juvenile rheumatoid arthritis (selected cases may require low-dose maintenance therapy)

Acute and subacute bursitis

Epicondylitis

Acute nonspecific tenosynovitis

Acute gouty arthritis

Psoriatic arthritis

Ankylosing spondylitis

• Collagen Diseases

During an exacerbation or as maintenance therapy in selected cases of:

Systemic lupus erythematosus

Acute rheumatic carditis

• Dermatologic Diseases

Pemphigus

Severe erythema multiforme (Stevens-Johnson syndrome)

Exfoliative dermatitis

Bullous dermatitis herpetiformis

Severe seborrheic dermatitis

Severe psoriasis

Mycosis fungoides

• Allergic States

Control of severe or incapacitating allergic conditions intractable to adequate trials of conventional treatment in:

Bronchial asthma

Contact dermatitis

Atopic dermatitis

Serum sickness

Seasonal or perennial allergic rhinitis

Drug hypersensitivity reactions

Urticarial transfusion reactions

Acute noninfectious laryngeal edema (epinephrine is the drug of first choice)

• Ophthalmic Diseases

Severe acute and chronic allergic and inflammatory processes involving the eye, such as:

Herpes zoster ophthalmicus

Iritis, iridocyclitis

Chorioretinitis

Diffuse posterior uveitis and choroiditis

Optic neuritis

Sympathetic ophthalmia

Anterior segment inflammation

Allergic conjunctivitis

Keratitis

Allergic corneal marginal ulcers

• Gastrointestinal Diseases

To tide the patient over a critical period of the disease in:

Ulcerative colitis (Systemic therapy)

Regional enteritis (Systemic therapy)

• Respiratory Diseases

Symptomatic sarcoidosis

Berylliosis

Fulminating or disseminated pulmonary tuberculosis when used concurrently with appropriate antituberculous chemotherapy Loeffler’s syndrome not manageable by other means

Aspiration pneumonitis

• Hematologic Disorders

Acquired (autoimmune) hemolytic anemia
Idiopathic thrombocytopenic purpura in adults (IV only; IM administration is contraindicated)

Secondary thrombocytopenia in adults

Erythroblastopenia (RBC anemia)

Congenital (erythroid) hypoplastic anemia

• Neoplastic Diseases

For palliative management of:

Leukemias and lymphomas in adults

Acute leukemia of childhood

• Edematous States

To induce diuresis or remission of proteinuria in the nephrotic syndrome, without uremia, of the idiopathic type, or that due to lupus erythematosus

• Miscellaneous

Tuberculous meningitis with subarachnoid block or impending block when used concurrently with appropriate antituberculous chemotherapy

Trichinosis with neurologic or myocardial involvement

• Diagnostic testing of adrenocortical hyperfunction

• Cerebral Edema associated with primary or metastatic brain tumor, craniotomy, or head injury.

Use in cerebral edema is not a substitute for careful neurosurgical evaluation and definitive management such as neurosurgery or other specific therapy.

By Intra-articular or Soft Tissue Injection

As adjunctive therapy for short-term administration (to tide the patient over an acute episode or exacerbation) in:

Synovitis of osteoarthritis

Rheumatoid arthritis

Acute and subacute bursitis

Acute gouty arthritis

Epicondylitis

Acute nonspecific tenosynovitis

Post-traumatic osteoarthritis

By Intralesional Injection

Keloids

Localized hypertrophic, infiltrated, inflammatory lesions of: lichen planus, psoriatic plaques, granuloma annulare and lichen simplex chronicus (neurodermatitis)

Discoid lupus erythematosus

Necrobiosis lipoidica diabeticorum

Alopecia areata

May also be useful in cystic tumors of an aponeurosis or tendon (ganglia)

CONTRAINDICATIONS:

Systemic fungal infections (see WARNINGS regarding amphotericin B). Hypersensitivity to any component of this product, including sulfites (see WARNINGS).

WARNINGS:

Because rare instances of anaphylactoid reactions have occurred in patients receiving parenteral corticosteroid therapy, appropriate precautionary measures should be taken prior to administration, especially when the patient has a history of allergy to any drug. Anaphylactoid and hypersensitivity reactions have been reported for dexamethasone sodium phosphate (see ADVERSE REACTIONS).

Dexamethasone sodium phosphate injection contains sodium bisulfite, a sulfite that may cause allergic-type reactions including anaphylactic symptoms and life-threatening or less severe asthmatic episodes in certain susceptible people. The overall prevalence of sulfite sensitivity in the general population is unknown and probably low. Sulfite sensitivity is seen more frequently in asthmatic than in non-asthmatic people.

Corticosteroids may exacerbate systemic fungal infections and therefore, should not be used in the presence of such infections unless they are needed to control drug reactions due to amphotericin B. Moreover, there have been cases reported in which concomitant use of amphotericin B and hydrocortisone was followed by cardiac enlargement and congestive failure.

In patients on corticosteroid therapy subjected to any unusual stress, increased dosage of rapidly acting corticosteroids before, during, and after the stressful situation is indicated.

Drug-induced secondary adrenocortical insufficiency may result from too rapid withdrawal of corticosteroids and may be minimized by gradual reduction of dosage. This type of relative insufficiency may persist for months after discontinuation of therapy; therefore, in any situation of stress occurring during that period, hormone therapy should be reinstituted. If the patient is receiving steroids already, dosage may have to be increased. Since mineralocorticoid secretion may be impaired, salt and/or a mineralocorticoid should be administered concurrently.

Corticosteroids may mask some signs of infection, and new infections may appear during their use. There may be decreased resistance and inability to localize infection when corticosteroids are used. Moreover, corticosteroids may affect the nitroblue-tetrazolium test for bacterial infection and produce false negative results.

In cerebral malaria, a double-blind trial has shown that the use of corticosteroids is associated with prolongation of coma and a higher incidence of pneumonia and gastrointestinal bleeding.

Corticosteroids may activate latent amebiasis. Therefore, it is recommended that latent or active amebiasis be ruled out before initiating corticosteroid therapy in any patient who has spent time in the tropics or any patient with unexplained diarrhea.

Prolonged use of corticosteroids may produce posterior subcapsular cataracts, glaucoma with possible damage to the optic nerves, and may enhance the establishment of secondary ocular infections due to fungi or viruses.

Average and large doses of cortisone or hydrocortisone can cause elevation of blood pressure, salt and water retention, and increased excretion of potassium. These effects are less likely to occur with the synthetic derivatives except when used in large doses. Dietary salt restriction and potassium supplementation may be necessary. All corticosteroids increase calcium excretion.

Administration of live virus vaccines, including smallpox, is contraindicated in individuals receiving immunosuppressive doses of corticosteroids. If inactivated viral or bacterial vaccines are administered to individuals receiving immunosuppressive doses of corticosteroids, the expected serum antibody response may not be obtained. However, immunization procedures may be undertaken in patients who are receiving corticosteroids as replacement therapy, e.g., for Addison’s disease.

Persons who are on drugs which suppress the immune system are more susceptible to infections than healthy individuals. Chickenpox and measles, for example, can have a more serious or even fatal course in non-immune children or adults on corticosteroids. In such children or adults who have not had these diseases, particular care should be taken to avoid exposure. How the dose, route and duration of corticosteroid administration affects the risk of developing a disseminated infection is not known. The contribution of the underlying disease and/or prior corticosteroid treatment to the risk is also not known. If exposed to chickenpox, prophylaxis with varicella zoster immune globulin (VZIG) may be indicated. If exposed to measles, prophylaxis with pooled intramuscular immunoglobulin (IG) may be indicated. (See the respective package inserts for complete VZIG and IG prescribing information). If chickenpox develops, treatment with antiviral agents may be considered.

The use of dexamethasone sodium phosphate in active tuberculosis should be restricted to those cases of fulminating or disseminated tuberculosis in which the corticosteroid is used for the management of the disease in conjunction with an appropriate antituberculous regimen.

If corticosteroids are indicated in patients with latent tuberculosis or tuberculin reactivity, close observation is necessary as reactivation of the disease may occur. During prolonged corticosteroid therapy, these patients should receive chemoprophylaxis.

Literature reports suggest an apparent association between use of corticosteroids and left ventricular free wall rupture after a recent myocardial infarction; therefore, therapy with corticosteroids should be used with great caution in these patients.

Serious Neurologic Adverse Reactions with Epidural Administration

Serious neurologic events, some resulting in death, have been reported with epidural injection of corticosteroids. Specific events reported include, but are not limited to, spinal cord infarction, paraplegia, quadriplegia, cortical blindness, and stroke. These serious neurologic events have been reported with and without use of fluoroscopy. The safety and effectiveness of epidural administration of corticosteroids has not been established, and corticosteroids are not approved for this use.

Pregnancy

Teratogenic Effects: Pregnancy Category C–

Since adequate human reproduction studies have not been done with corticosteroids, use of these drugs in pregnancy or in women of childbearing potential requires that the anticipated benefits be weighed against the possible hazards to the mother and embryo or fetus. Infants born of mothers who have received substantial doses of corticosteroids during pregnancy should be carefully observed for signs of hypoadrenalism.

Corticosteroids appear in breast milk and could suppress growth, interfere with endogenous corticosteroid production, or cause other unwanted effects. Mothers taking pharmacologic doses of corticosteroids should be advised not to nurse.

PRECAUTIONS:

This product, like many other steroid formulations, is sensitive to heat. Therefore, it should not be autoclaved when it is desirable to sterilize the exterior of the vial.

Following prolonged therapy, withdrawal of corticosteroids may result in symptoms of the corticosteroid withdrawal syndrome including fever, myalgia, arthralgia, and malaise. This may occur in patients even without evidence of adrenal insufficiency.

There is an enhanced effect of corticosteroids in patients with hypothyroidism and in those with cirrhosis.

Corticosteroids should be used cautiously in patients with ocular herpes simplex for fear of corneal perforation.

The lowest possible dose of corticosteroid should be used to control the condition under treatment, and when reduction in dosage is possible, the reduction must be gradual.

Psychic derangements may appear when corticosteroids are used, ranging from euphoria, insomnia, mood swings, personality changes, and severe depression to frank psychotic manifestations. Also, existing emotional instability or psychotic tendencies may be aggravated by corticosteroids.

Aspirin should be used cautiously in conjunction with corticosteroids in hypoprothrombinemia.

Steroids should be used with caution in nonspecific ulcerative colitis, if there is a probability of impending perforation, abscess, or other pyogenic infection, also in diverticulitis, fresh intestinal anastomoses, active or latent peptic ulcer, renal insufficiency, hypertension, osteoporosis, and myasthenia gravis. Signs of peritoneal irritation following gastrointestinal perforation in patients receiving large doses of corticosteroids may be minimal or absent. Fat embolism has been reported as a possible complication of hypercortisonism.

When large doses are given, some authorities advise that antacids be administered between meals to help to prevent peptic ulcer.

Growth and development of infants and children on prolonged corticosteroid therapy should be carefully followed.

Steroids may increase or decrease motility and number of spermatozoa in some patients.

Phenytoin, phenobarbital, ephedrine, and rifampin may enhance the metabolic clearance of corticosteroids resulting in decreased blood levels and lessened physiologic activity, thus requiring adjustment in corticosteroid dosage. These interactions may interfere with dexamethasone suppression tests which should be interpreted with caution during administration of these drugs.

False negative results in the dexamethasone suppression test (DST) in patients being treated with indomethacin have been reported. Thus, results of the DST should be interpreted with caution in these patients.

The prothrombin time should be checked frequently in patients who are receiving corticosteroids and coumarin anticoagulants at the same time because of reports that corticosteroids have altered the response to these anticoagulants. Studies have shown that the usual effect produced by adding corticosteroids is inhibition of response to coumarins, although there have been some conflicting reports of potentiation not substantiated by studies.

When corticosteroids are administered concomitantly with potassium-depleting diuretics, patients should be observed closely for development of hypokalemia.

Intra-articular injection of a corticosteroid may produce systemic as well as local effects.

Appropriate examination of any joint fluid present is necessary to exclude a septic process.

A marked increase in pain accompanied by local swelling, further restriction of joint motion, fever, and malaise is suggestive of septic arthritis. If this complication occurs and the diagnosis of sepsis is confirmed, appropriate antimicrobial therapy should be instituted.

Injection of a steroid into an infected site is to be avoided.

Corticosteroids should not be injected into unstable joints.

Patients should be impressed strongly with the importance of not overusing joints in which symptomatic benefit has been obtained as long as the inflammatory process remains active.

Frequent intra-articular injection may result in damage to joint tissues.

The slower rate of absorption by intramuscular administration should be recognized.

Information for Patients

Persons who are on immunosuppressant doses of corticosteroids should be warned to avoid exposure to chickenpox or measles. Patients should also be advised that if they are exposed, medical advice should be sought without delay.

ADVERSE REACTIONS:

Fluid and electrolyte disturbances:

Sodium retention

Fluid retention

Congestive heart failure in susceptible patients

Potassium loss

Hypokalemic alkalosis

Hypertension

Musculoskeletal:

Muscle weakness

Steroid myopathy

Loss of muscle mass

Osteoporosis

Pathologic fracture of long bones

Vertebral compression fractures

Aseptic necrosis of femoral and humeral heads

Tendon rupture

Gastrointestinal:

Peptic ulcer with possible subsequent perforation and hemorrhage

Perforation of the small and large bowel, particularly in patients with inflammatory bowel disease

Pancreatitis

Abdominal distention

Ulcerative esophagitis

Dermatologic:

Impaired wound healing

Thin fragile skin

Petechiae and ecchymoses

Erythema

Increased sweating

May suppress reactions to skin tests

Burning or tingling, especially in the perineal area (after IV injection)

Other cutaneous reactions, such as allergic dermatitis, urticaria, angioneurotic edema

Neurologic:

Convulsions

Increased intracranial pressure with papilledema (pseudotumor cerebri) usually after treatment

Vertigo

Headache

Psychic disturbances

Endocrine:

Menstrual irregularities

Development of cushingoid state

Suppression of growth in children

Secondary adrenocortical and pituitary unresponsiveness, particularly in times of stress, as in trauma, surgery, or illness

Decreased carbohydrate tolerance

Manifestations of latent diabetes mellitus

Increased requirements for insulin or oral hypoglycemic agents in diabetics

Hirsutism

Ophthalmic:

Posterior subcapsular cataracts

Increased intraocular pressure

Glaucoma

Exophthalmos

Metabolic:

Negative nitrogen balance due to protein catabolism

Cardiovascular:

Myocardial rupture following recent myocardial infarction (see WARNINGS)

Other:

Anaphylactoid or hypersensitivity reactions

Thromboembolism

Weight gain

Increased appetite

Nausea

Malaise

Hiccups

The following additional adverse reactions are related to parenteral corticosteroid therapy:

Rare instances of blindness associated with intralesional therapy around the face and head

Hyperpigmentation or hypopigmentation

Subcutaneous and cutaneous atrophy

Sterile abscess

Post-injection flare (following intra-articular use)

Charcot-like arthropathy

OVERDOSAGE:

Reports of acute toxicity and/or death following overdosage of glucocorticoids are rare. In the event of overdosage, no specific antidote is available; treatment is supportive and symptomatic.

The oral LD50 of dexamethasone in female mice was 6.5 g/kg. The intravenous LD50 of dexamethasone sodium phosphate in female mice was 794 mg/kg.

DOSAGE AND ADMINISTRATION:

Dexamethasone sodium phosphate injection, 4 mg per mL– For intravenous, intramuscular, intra-articular, intralesional, and soft tissue injection.

Dexamethasone sodium phosphate injection can be given directly from the vial, or it can be added to Sodium Chloride Injection or Dextrose Injection and administered by intravenous drip.

Solutions used for intravenous administration or further dilution of this product should be preservative free when used in the neonate, especially the premature infant.

When it is mixed with an infusion solution, sterile precautions should be observed. Since infusion solutions generally do not contain preservatives, mixtures should be used within 24 hours.

DOSAGE REQUIREMENTS ARE VARIABLE AND MUST BE INDIVIDUALIZED ON THE BASIS OF THE DISEASE AND THE RESPONSE OF THE PATIENT.

Intravenous and Intramuscular Injection:

The initial dosage of dexamethasone sodium phosphate injection varies from 0.5 to 9 mg a day depending on the disease being treated. In less severe diseases doses lower than 0.5 mg may suffice, while in severe diseases doses higher than 9 mg may be required.

The initial dosage should be maintained or adjusted until the patient’s response is satisfactory. If a satisfactory clinical response does not occur after a reasonable period of time, discontinue dexamethasone sodium phosphate injection and transfer the patient to other therapy.

After a favorable initial response, the proper maintenance dosage should be determined by decreasing the initial dosage in small amounts to the lowest dosage that maintains an adequate clinical response.

Patients should be observed closely for signs that might require dosage adjustment, including changes in clinical status resulting from remissions or exacerbations of the disease, individual drug responsiveness, and the effect of stress (e.g., surgery, infection, trauma). During stress it may be necessary to increase dosage temporarily.

If the drug is to be stopped after more than a few days of treatment, it usually should be withdrawn gradually.

When the intravenous route of administration is used, dosage usually should be the same as the oral dosage. In certain overwhelming, acute, life-threatening situations, however, administration in dosages exceeding the usual dosages may be justified and may be in multiples of the oral dosages. The slower rate of absorption by intramuscular administration should be recognized.

Shock

There is a tendency in current medical practice to use high (pharmacologic) doses of corticosteroids for the treatment of unresponsive shock. The following dosages of dexamethasone sodium phosphate injection have been suggested by various authors:

Author | Dosage
Cavanagh^1 | 3 mg/kg of body weight per 24 hours by constant intravenous infusion after an initial intravenous injection of 20 mg
Dietzman^2 | 2 to 6 mg/kg of bodyweight as a single intravenous injection
Frank^3 | 40 mg initially followed by repeat intravenous injection every 4 to 6 hours while shock persists
Oaks^4 | 40 mg initially followed by repeat intravenous injection every 2 to 6 hours while shock persists
Schumer^5 | 1 mg/kg of body weight as a single intravenous injection

Administration of high dose corticosteroid therapy should be continued only until the patients condition has stabilized and usually not longer than 48 to 72 hours.

Although adverse reactions associated with high dose, short term corticosteroid therapy are uncommon, peptic ulceration may occur.

Cerebral Edema

Dexamethasone sodium phosphate injection is generally administered initially in a dosage of 10 mg intravenously followed by four mg every six hours intramuscularly until the symptoms of cerebral edema subside. Response is usually noted within 12 to 24 hours and dosage may be reduced after two to four days and gradually discontinued over a period of five to seven days. For palliative management of patients with recurrent or inoperable brain tumors, maintenance therapy with two mg two or three times a day may be effective.

Acute Allergic Disorders

In acute, self-limited allergic disorders or acute exacerbations of chronic allergic disorders, the following dosage schedule combining parenteral and oral therapy is suggested:

Dexamethasone sodium phosphate injection, 4 mg per mL: first day, 1 or 2 mL (4 or 8 mg), intramuscularly.

Dexamethasone tablets, 0.75 mg: second and third days, 4 tablets in two divided doses each day; fourth day, 2 tablets in two divided doses; fifth and sixth days, 1 tablet each day; seventh day, no treatment; eighth day, follow-up visit.

This schedule is designed to ensure adequate therapy during acute episodes, while minimizing the risk of overdosage in chronic cases.

Intra-articular, Intralesional and Soft Tissue Injection

Intra-articular, intralesional, and soft tissue injections are generally employed when the affected joints or areas are limited to one or two sites. Dosage and frequency of injection varies depending on the condition and the site of injection. The usual dose is from 0.2 to 6 mg. The frequency usually ranges from once every three to five days to once every two to three weeks. Frequent intra-articular injection may result in damage to joint tissues.

Some of the usual single doses are:

Site of Injection | Amount of Dexamethasone Phosphate (mg)
Large Joints (e.g., Knee) | 2 to 4
Small Joints (e.g., Interphalangeal, Temporomandibular) | 0.8 to 1
Bursae | 2 to 3
Tendon Sheaths | 0.4 to 1
Soft Tissue Infiltration | 2 to 6
Ganglia | 1 to 2

Dexamethasone sodium phosphate injection is particularly recommended for use in conjunction with one of the less soluble, longer-acting steroids for intra-articular and soft tissue injection.

Parenteral drug products should be inspected visually for particulate matter and discoloration prior to administration, whenever the solution and container permit.

HOW SUPPLIED:

Product No. | NDC No.
16501 | 63323-165-01 | Dexamethasone Sodium Phosphate Injection, USP (equivalent to 4 mg per mL dexamethasone phosphate) 1 mL fill, in a 2 mL flip-top vial, packaged in 25.

STORE AT:20° to 25°C (68° to 77°F) [see USP Controlled Room Temperature]. Protect from freezing. Sensitive to heat. Do not autoclave.

Protect from light. Store container in carton until contents have been used.

Do not use if precipitate is present.

www.fresenius-kabi.us

45799H

Revised: March 2017

REFERENCES:

1. Cavanagh, D.; Singh, K.B.: Endotoxin shock in pregnancy and abortion, in: “Corticosteroids in the Treatment of Shock”, Schumer, W.; Nyhus, L.M., Editors, Urbana, University of Illinois Press, 1970, pp. 86-96.
2. Dietzman, R.H.; Ersek, R.A.; Bloch, J.M.; Lillehei, R.C.: High-output, low-resistance gram-negative septic shock in man, Angiology 20: 691-700, Dec. 1969.
3. Frank, E.: Clinical observations in shock and management (In: Shields, T.F., ed.: Symposium on current concepts and management of shock), J. Maine Med. Ass. 59: 195-200, Oct. 1968.
4. Oaks, W. W.; Cohen, H.E.: Endotoxin shock in the geriatric patient, Geriat. 22: 120-130, Mar. 1967.
5. Schumer, W.; Nyhus, L.M.: Corticosteroid effect on biochemical parameters of human oligemic shock, Arch. Surg. 100: 405-408, Apr. 1970.

MarcaineTM

Bupivacaine Hydrochloride Injection, USP

Rx only

DESCRIPTION

Bupivacaine hydrochloride is 2-Piperidinecarboxamide, 1-butyl-N-(2,6-dimethylphenyl)-, monohydrochloride, monohydrate, a white crystalline powder that is freely soluble in 95 percent ethanol, soluble in water, and slightly soluble in chloroform or acetone. It has the following structural formula:

MARCAINE is available in sterile isotonic solutions with and without epinephrine (as bitartrate) 1:200,000 for injection via local infiltration, peripheral nerve block, and caudal and lumbar epidural blocks. Solutions of MARCAINE may be autoclaved if they do not contain epinephrine. Solutions are clear and colorless.

Bupivacaine is related chemically and pharmacologically to the aminoacyl local anesthetics. It is a homologue of mepivacaine and is chemically related to lidocaine. All three of these anesthetics contain an amide linkage between the aromatic nucleus and the amino, or piperidine group. They differ in this respect from the procaine-type local anesthetics, which have an ester linkage.

MARCAINE—Sterile isotonic solutions containing sodium chloride. In multiple-dose vials, each mL also contains 1 mg methylparaben as antiseptic preservative. The pH of these solutions is adjusted to between 4 and 6.5 with sodium hydroxide or hydrochloric acid.

CLINICAL PHARMACOLOGY

Local anesthetics block the generation and the conduction of nerve impulses, presumably by increasing the threshold for electrical excitation in the nerve, by slowing the propagation of the nerve impulse, and by reducing the rate of rise of the action potential. In general, the progression of anesthesia is related to the diameter, myelination, and conduction velocity of affected nerve fibers. Clinically, the order of loss of nerve function is as follows: (1) pain, (2) temperature, (3) touch, (4) proprioception, and (5) skeletal muscle tone.

Systemic absorption of local anesthetics produces effects on the cardiovascular and central nervous systems (CNS). At blood concentrations achieved with normal therapeutic doses, changes in cardiac conduction, excitability, refractoriness, contractility, and peripheral vascular resistance are minimal. However, toxic blood concentrations depress cardiac conduction and excitability, which may lead to atrioventricular block, ventricular arrhythmias, and cardiac arrest, sometimes resulting in fatalities. In addition, myocardial contractility is depressed and peripheral vasodilation occurs, leading to decreased cardiac output and arterial blood pressure. Recent clinical reports and animal research suggest that these cardiovascular changes are more likely to occur after unintended intravascular injection of bupivacaine. Therefore, incremental dosing is necessary.

Following systemic absorption, local anesthetics can produce central nervous system stimulation, depression, or both. Apparent central stimulation is manifested as restlessness, tremors and shivering progressing to convulsions, followed by depression and coma progressing ultimately to respiratory arrest. However, the local anesthetics have a primary depressant effect on the medulla and on higher centers. The depressed stage may occur without a prior excited state.

Pharmacokinetics: The rate of systemic absorption of local anesthetics is dependent upon the total dose and concentration of drug administered, the route of administration, the vascularity of the administration site, and the presence or absence of epinephrine in the anesthetic solution.

The onset of action with MARCAINE is rapid and anesthesia is long lasting. The duration of anesthesia is significantly longer with MARCAINE than with any other commonly used local anesthetic. It has also been noted that there is a period of analgesia that persists after the return of sensation, during which time the need for strong analgesics is reduced.

The onset of action following dental injections is usually 2 to 10 minutes and anesthesia may last two or three times longer than lidocaine and mepivacaine for dental use, in many patients up to 7 hours.

Local anesthetics are bound to plasma proteins in varying degrees. Generally, the lower the plasma concentration of drug the higher the percentage of drug bound to plasma proteins.

Local anesthetics appear to cross the placenta by passive diffusion. The rate and degree of diffusion is governed by (1) the degree of plasma protein binding, (2) the degree of ionization, and (3) the degree of lipid solubility. Fetal/ maternal ratios of local anesthetics appear to be inversely related to the degree of plasma protein binding, because only the free, unbound drug is available for placental transfer. MARCAINE with a high protein binding capacity (95%) has a low fetal/maternal ratio (0.2 to 0.4). The extent of placental transfer is also determined by the degree of ionization and lipid solubility of the drug. Lipid soluble, nonionized drugs readily enter the fetal blood from the maternal circulation.

Depending upon the route of administration, local anesthetics are distributed to some extent to all body tissues, with high concentrations found in highly perfused organs such as the liver, lungs, heart, and brain.

Pharmacokinetic studies on the plasma profile of MARCAINE after direct intravenous injection suggest a three-compartment open model. The first compartment is represented by the rapid intravascular distribution of the drug. The second compartment represents the equilibration of the drug throughout the highly perfused organs such as the brain, myocardium, lungs, kidneys, and liver. The third compartment represents an equilibration of the drug with poorly perfused tissues, such as muscle and fat. The elimination of drug from tissue distribution depends largely upon the ability of binding sites in the circulation to carry it to the liver where it is metabolized.

After injection of MARCAINE for caudal, epidural, or peripheral nerve block in man, peak levels of bupivacaine in the blood are reached in 30 to 45 minutes, followed by a decline to insignificant levels during the next three to six hours.

Various pharmacokinetic parameters of the local anesthetics can be significantly altered by the presence of hepatic or renal disease, factors affecting urinary pH, renal blood flow, the route of drug administration, and the age of the patient. The half-life of MARCAINE in adults is 2.7 hours and in neonates 8.1 hours.

In clinical studies, elderly patients reached the maximal spread of analgesia and maximal motor blockade more rapidly than younger patients. Elderly patients also exhibited higher peak plasma concentrations following administration of this product. The total plasma clearance was decreased in these patients.

Amide-type local anesthetics such as MARCAINE are metabolized primarily in the liver via conjugation with glucuronic acid. Patients with hepatic disease, especially those with severe hepatic disease, may be more susceptible to the potential toxicities of the amide-type local anesthetics. Pipecoloxylidine is the major metabolite of MARCAINE.

The kidney is the main excretory organ for most local anesthetics and their metabolites. Urinary excretion is affected by urinary perfusion and factors affecting urinary pH. Only 6% of bupivacaine is excreted unchanged in the urine.

When administered in recommended doses and concentrations, MARCAINE does not ordinarily produce irritation or tissue damage and does not cause methemoglobinemia.

INDICATIONS AND USAGE

MARCAINE is indicated for the production of local or regional anesthesia or analgesia for surgery, dental and oral surgery procedures, diagnostic and therapeutic procedures, and for obstetrical procedures. Only the 0.25% and 0.5% concentrations are indicated for obstetrical anesthesia. (See WARNINGS.)

Experience with nonobstetrical surgical procedures in pregnant patients is not sufficient to recommend use of 0.75% concentration of MARCAINE in these patients.

MARCAINE is not recommended for intravenous regional anesthesia (Bier Block). See WARNINGS.

The routes of administration and indicated MARCAINE concentrations are:

•local infiltration 0.25%
•peripheral nerve block 0.25% and 0.5%
•retrobulbar block 0.75%
•sympathetic block 0.25%
•lumbar epidural 0.25%, 0.5%, and 0.75%

(0.75% not for obstetrical anesthesia)
•caudal 0.25% and 0.5%

(See DOSAGE AND ADMINISTRATION for additional information).

Standard textbooks should be consulted to determine the accepted procedures and techniques for the administration of MARCAINE.

CONTRAINDICATIONS

MARCAINE is contraindicated in obstetrical paracervical block anesthesia. Its use in this technique has resulted in fetal bradycardia and death.

MARCAINE is contraindicated in patients with a known hypersensitivity to it or to any local anesthetic agent of the amide-type or to other components of MARCAINE solutions.

WARNINGS

THE 0.75% CONCENTRATION OF MARCAINE IS NOT RECOMMENDED FOR OBSTETRICAL ANESTHESIA. THERE HAVE BEEN REPORTS OF CARDIAC ARREST WITH DIFFICULT RESUSCITATION OR DEATH DURING USE OF MARCAINE FOR EPIDURAL ANESTHESIA IN OBSTETRICAL PATIENTS. IN MOST CASES, THIS HAS FOLLOWED USE OF THE 0.75% CONCENTRATION. RESUSCITATION HAS BEEN DIFFICULT OR IMPOSSIBLE DESPITE APPARENTLY ADEQUATE PREPARATION AND APPROPRIATE MANAGEMENT. CARDIAC ARREST HAS OCCURRED AFTER CONVULSIONS RESULTING FROM SYSTEMIC TOXICITY, PRESUMABLY FOLLOWING UNINTENTIONAL INTRAVASCULAR INJECTION. THE 0.75% CONCENTRATION SHOULD BE RESERVED FOR SURGICAL PROCEDURES WHERE A HIGH DEGREE OF MUSCLE RELAXATION AND PROLONGED EFFECT ARE NECESSARY.

LOCAL ANESTHETICS SHOULD ONLY BE EMPLOYED BY CLINICIANS WHO ARE WELL VERSED IN DIAGNOSIS AND MANAGEMENT OF DOSE-RELATED TOXICITY AND OTHER ACUTE EMERGENCIES WHICH MIGHT ARISE FROM THE BLOCK TO BE EMPLOYED, AND THEN ONLY AFTER INSURING THE IMMEDIATE AVAILABILITY OF OXYGEN, OTHER RESUSCITATIVE DRUGS, CARDIOPULMONARY RESUSCITATIVE EQUIPMENT, AND THE PERSONNEL RESOURCES NEEDED FOR PROPER MANAGEMENT OF TOXIC REACTIONS AND RELATED EMERGENCIES. (See also ADVERSE REACTIONS, PRECAUTIONS, and OVERDOSAGE.) DELAY IN PROPER MANAGEMENT OF DOSE-RELATED TOXICITY, UNDERVENTILATION FROM ANY CAUSE, AND/OR ALTERED SENSITIVITY MAY LEAD TO THE DEVELOPMENT OF ACIDOSIS, CARDIAC ARREST AND, POSSIBLY, DEATH.

Local anesthetic solutions containing antimicrobial preservatives, i.e., those supplied in multiple-dose vials, should not be used for epidural or caudal anesthesia because safety has not been established with regard to intrathecal injection, either intentionally or unintentionally, of such preservatives.

Intra-articular infusions of local anesthetics following arthroscopic and other surgical procedures is an unapproved use, and there have been post-marketing reports of chondrolysis in patients receiving such infusions. The majority of reported cases of chondrolysis have involved the shoulder joint; cases of gleno-humeral chondrolysis have been described in pediatric and adult patients following intra-articular infusions of local anesthetics with and without epinephrine for periods of 48 to 72 hours. There is insufficient information to determine whether shorter infusion periods are not associated with these findings. The time of onset of symptoms, such as joint pain, stiffness and loss of motion can be variable, but may begin as early as the 2nd month after surgery. Currently, there is no effective treatment for chondrolysis; patients who experienced chondrolysis have required additional diagnostic and therapeutic procedures and some required arthroplasty or shoulder replacement.

It is essential that aspiration for blood or cerebrospinal fluid (where applicable) be done prior to injecting any local anesthetic, both the original dose and all subsequent doses, to avoid intravascular or subarachnoid injection. However, a negative aspiration does not ensure against an intravascular or subarachnoid injection.

Until further experience is gained in pediatric patients younger than 12 years, administration of MARCAINE in this age group is not recommended.

Mixing or the prior or intercurrent use of any other local anesthetic with MARCAINE cannot be recommended because of insufficient data on the clinical use of such mixtures.

There have been reports of cardiac arrest and death during the use of MARCAINE for intravenous regional anesthesia (Bier Block). Information on safe dosages and techniques of administration of MARCAINE in this procedure is lacking. Therefore, MARCAINE is not recommended for use in this technique.

Single-dose ampuls and single-dose vials of MARCAINE without epinephrine do not contain sodium metabisulfite.

PRECAUTIONS

GENERAL PRECAUTIONS

General: The safety and effectiveness of local anesthetics depend on proper dosage, correct technique, adequate precautions, and readiness for emergencies. Resuscitative equipment, oxygen, and other resuscitative drugs should be available for immediate use (See WARNINGS, ADVERSE REACTIONS, and OVERDOSAGE). During major regional nerve blocks, the patient should have intravenous fluids running via an indwelling catheter to assure a functioning intravenous pathway. The lowest dosage of local anesthetic that results in effective anesthesia should be used to avoid high plasma levels and serious adverse effects. The rapid injection of a large volume of local anesthetic solution should be avoided and fractional (incremental) doses should be used when feasible.

Epidural Anesthesia: During epidural administration of MARCAINE, 0.5% and 0.75% solutions should be administered in incremental doses of 3 mL to 5 mL with sufficient time between doses to detect toxic manifestations of unintentional intravascular or intrathecal injection. Injections should be made slowly, with frequent aspirations before and during the injection to avoid intravascular injection. Syringe aspirations should also be performed before and during each supplemental injection in continuous (intermittent) catheter techniques. An intravascular injection is still possible even if aspirations for blood are negative.

During the administration of epidural anesthesia, it is recommended that a test dose be administered initially and the effects monitored before the full dose is given. When using a "continuous" catheter technique, test doses should be given prior to both the original and all reinforcing doses, because plastic tubing in the epidural space can migrate into a blood vessel or through the dura.

The sedated patient may exhibit only a pulse rate increase of 20 or more beats per minute for 15 or more seconds. Therefore, following the test dose, the heart rate should be monitored for a heart rate increase. Patients on beta-blockers may not manifest changes in heart rate, but blood pressure monitoring can detect a transient rise in systolic blood pressure. The test dose should also contain 10 mg to 15 mg of MARCAINE or an equivalent amount of another local anesthetic to detect an unintended intrathecal administration. This will be evidenced within a few minutes by signs of spinal block (e.g., decreased sensation of the buttocks, paresis of the legs, or, in the sedated patient, absent knee jerk).

Injection of repeated doses of local anesthetics may cause significant increases in plasma levels with each repeated dose due to slow accumulation of the drug or its metabolites, or to slow metabolic degradation. Tolerance to elevated blood levels varies with the status of the patient. Debilitated, elderly patients and acutely ill patients should be given reduced doses commensurate with their age and physical status. Local anesthetics should also be used with caution in patients with hypotension or heartblock.

Careful and constant monitoring of cardiovascular and respiratory (adequacy of ventilation) vital signs and the patient's state of consciousness should be performed after each local anesthetic injection. It should be kept in mind at such times that restlessness, anxiety, incoherent speech, lightheadedness, numbness and tingling of the mouth and lips, metallic taste, tinnitus, dizziness, blurred vision, tremors, twitching, depression, or drowsiness may be early warning signs of central nervous system toxicity.

Local anesthetic solutions containing a vasoconstrictor should be used cautiously and in carefully restricted quantities in areas of the body supplied by end arteries or having otherwise compromised blood supply such as digits, nose, external ear, or penis. Patients with hypertensive vascular disease may exhibit exaggerated vasoconstrictor response. Ischemic injury or necrosis may result.

Because amide-local anesthetics such as MARCAINE are metabolized by the liver, these drugs, especially repeat doses, should be used cautiously in patients with hepatic disease. Patients with severe hepatic disease, because of their inability to metabolize local anesthetics normally, are at a greater risk of developing toxic plasma concentrations. Local anesthetics should also be used with caution in patients with impaired cardiovascular function because they may be less able to compensate for functional changes associated with the prolongation of AV conduction produced by these drugs.

Many drugs used during the conduct of anesthesia are considered potential triggering agents for familial malignant hyperthermia. Because it is not known whether amide-type local anesthetics may trigger this reaction and because the need for supplemental general anesthesia cannot be predicted in advance, it is suggested that a standard protocol for management should be available. Early unexplained signs of tachycardia, tachypnea, labile blood pressure, and metabolic acidosis may precede temperature elevation. Successful outcome is dependent on early diagnosis, prompt discontinuance of the suspect triggering agent(s) and prompt institution of treatment, including oxygen therapy, indicated supportive measures and dantrolene (Consult dantrolene sodium intravenous package insert before using).

Use in Head and Neck Area: Small doses of local anesthetics injected into the head and neck area, including retrobulbar, dental, and stellate ganglion blocks, may produce adverse reactions similar to systemic toxicity seen with unintentional intravascular injections of larger doses. The injection procedures require the utmost care. Confusion, convulsions, respiratory depression, and/or respiratory arrest, and cardiovascular stimulation or depression have been reported. These reactions may be due to intra-arterial injection of the local anesthetic with retrograde flow to the cerebral circulation. They may also be due to puncture of the dural sheath of the optic nerve during retrobulbar block with diffusion of any local anesthetic along the subdural space to the midbrain. Patients receiving these blocks should have their circulation and respiration monitored and be constantly observed. Resuscitative equipment and personnel for treating adverse reactions should be immediately available. Dosage recommendations should not be exceeded (See DOSAGE AND ADMINISTRATION).

Use in Ophthalmic Surgery: Clinicians who perform retrobulbar blocks should be aware that there have been reports of respiratory arrest following local anesthetic injection. Prior to retrobulbar block, as with all other regional procedures, the immediate availability of equipment, drugs, and personnel to manage respiratory arrest or depression, convulsions, and cardiac stimulation or depression should be assured (see also WARNINGS and Use In Head and Neck Area, above). As with other anesthetic procedures, patients should be constantly monitored following ophthalmic blocks for signs of these adverse reactions, which may occur following relatively low total doses.

PATIENT COUNSELING INFORMATION

Information for Patients: When appropriate, patients should be informed in advance that they may experience temporary loss of sensation and motor activity, usually in the lower half of the body, following proper administration of caudal or epidural anesthesia. Also, when appropriate, the physician should discuss other information including adverse reactions in the package insert of MARCAINE.

Patients receiving dental injections of MARCAINE should be cautioned not to chew solid foods or test the anesthetized area by biting or probing until anesthesia has worn off (up to 7 hours).

DRUG INTERACTIONS

Clinically Significant Drug Interactions:The administration of local anesthetic solutions containing epinephrine or norepinephrine to patients receiving monoamine oxidase inhibitors or tricyclic antidepressants may produce severe, prolonged hypertension. Concurrent use of these agents should generally be avoided. In situations when concurrent therapy is necessary, careful patient monitoring is essential.

Concurrent administration of vasopressor drugs and of ergot-type oxytocic drugs may cause severe, persistent hypertension or cerebrovascular accidents.

CARCINOGENESIS AND MUTAGENESIS AND IMPAIRMENT OF FERTILITY

Carcinogenesis, Mutagenesis, Impairment of Fertility: Long-term studies in animals to evaluate the carcinogenic potential of bupivacaine hydrochloride have not been conducted. The mutagenic potential and the effect on fertility of bupivacaine hydrochloride have not been determined.

PREGNANCY

Pregnancy: There are no adequate and well-controlled studies in pregnant women. MARCAINE should be used during pregnancy only if the potential benefit justifies the potential risk to the fetus. Bupivacaine hydrochloride produced developmental toxicity when administered subcutaneously to pregnant rats and rabbits at clinically relevant doses. This does not exclude the use of MARCAINE at term for obstetrical anesthesia or analgesia (See Labor and Delivery).

Bupivacaine hydrochloride was administered subcutaneously to rats at doses of 4.4, 13.3, & 40 mg/kg and to rabbits at doses of 1.3, 5.8, & 22.2 mg/kg during the period of organogenesis (implantation to closure of the hard palate). The high doses are comparable to the daily maximum recommended human dose (MRHD) of 400 mg/day on a mg/m2 body surface area (BSA) basis. No embryo-fetal effects were observed in rats at the high dose which caused increased maternal lethality. An increase in embryo-fetal deaths was observed in rabbits at the high dose in the absence of maternal toxicity with the fetal No Observed Adverse Effect Level representing approximately 1/5th the MRHD on a BSA basis.

In a rat pre- and post-natal development study (dosing from implantation through weaning) conducted at subcutaneous doses of 4.4, 13.3, & 40 mg/kg, decreased pup survival was observed at the high dose. The high dose is comparable to the daily MRHD of 400 mg/day on a BSA basis.

Labor and Delivery: SEE BOXED WARNING REGARDING OBSTETRICAL USE OF 0.75% MARCAINE.

MARCAINE is contraindicated for obstetrical paracervical block anesthesia.

Local anesthetics rapidly cross the placenta, and when used for epidural, caudal, or pudendal block anesthesia, can cause varying degrees of maternal, fetal, and neonatal toxicity (See CLINICAL PHARMACOLOGY, Pharmacokinetics). The incidence and degree of toxicity depend upon the procedure performed, the type, and amount of drug used, and the technique of drug administration. Adverse reactions in the parturient, fetus, and neonate involve alterations of the central nervous system, peripheral vascular tone, and cardiac function.

Maternal hypotension has resulted from regional anesthesia. Local anesthetics produce vasodilation by blocking sympathetic nerves. Elevating the patient's legs and positioning her on her left side will help prevent decreases in blood pressure. The fetal heart rate also should be monitored continuously and electronic fetal monitoring is highly advisable.

Epidural, caudal, or pudendal anesthesia may alter the forces of parturition through changes in uterine contractility or maternal expulsive efforts. Epidural anesthesia has been reported to prolong the second stage of labor by removing the parturient's reflex urge to bear down or by interfering with motor function. The use of obstetrical anesthesia may increase the need for forceps assistance.

The use of some local anesthetic drug products during labor and delivery may be followed by diminished muscle strength and tone for the first day or two of life. This has not been reported with bupivacaine.

It is extremely important to avoid aortocaval compression by the gravid uterus during administration of regional block to parturients. To do this, the patient must be maintained in the left lateral decubitus position or a blanket roll or sandbag may be placed beneath the right hip and gravid uterus displaced to the left.

NURSING MOTHERS

Nursing Mothers: Bupivacaine has been reported to be excreted in human milk suggesting that the nursing infant could be theoretically exposed to a dose of the drug. Because of the potential for serious adverse reactions in nursing infants from bupivacaine, a decision should be made whether to discontinue nursing or not administer bupivacaine, taking into account the importance of the drug to the mother.

PEDIATRIC USE

Pediatric Use: Until further experience is gained in pediatric patients younger than 12 years, administration of MARCAINE in this age group is not recommended. Continuous infusions of bupivacaine in children have been reported to result in high systemic levels of bupivacaine and seizures; high plasma levels may also be associated with cardiovascular abnormalities (See WARNINGS, PRECAUTIONS, and OVERDOSAGE).

GERIATRIC USE

Geriatric Use: Patients over 65 years, particularly those with hypertension, may be at increased risk for developing hypotension while undergoing anesthesia with MARCAINE (See ADVERSE REACTIONS).

Elderly patients may require lower doses of MARCAINE (See PRECAUTIONS, Epidural Anesthesia and DOSAGE AND ADMINISTRATION).

In clinical studies, differences in various pharmacokinetic parameters have been observed between elderly and younger patients (See CLINICAL PHARMACOLOGY).

This product is known to be substantially excreted by the kidney, and the risk of toxic reactions to this drug may be greater in patients with impaired renal function. Because elderly patients are more likely to have decreased renal function, care should be taken in dose selection, and it may be useful to monitor renal function (See CLINICAL PHARMACOLOGY).

ADVERSE REACTIONS

Reactions to MARCAINE are characteristic of those associated with other amide-type local anesthetics. A major cause of adverse reactions to this group of drugs is excessive plasma levels, which may be due to overdosage, unintentional intravascular injection, or slow metabolic degradation.

The most commonly encountered acute adverse experiences which demand immediate counter-measures are related to the central nervous system and the cardiovascular system. These adverse experiences are generally dose related and due to high plasma levels which may result from overdosage, rapid absorption from the injection site, diminished tolerance, or from unintentional intravascular injection of the local anesthetic solution. In addition to systemic dose-related toxicity, unintentional subarachnoid injection of drug during the intended performance of caudal or lumbar epidural block or nerve blocks near the vertebral column (especially in the head and neck region) may result in underventilation or apnea ("Total or High Spinal"). Also, hypotension due to loss of sympathetic tone and respiratory paralysis or underventilation due to cephalad extension of the motor level of anesthesia may occur. This may lead to secondary cardiac arrest if untreated. Patients over 65 years, particularly those with hypertension, may be at increased risk for experiencing the hypotensive effects of MARCAINE. Factors influencing plasma protein binding, such as acidosis, systemic diseases which alter protein production, or competition of other drugs for protein binding sites, may diminish individual tolerance.

Central Nervous System Reactions: These are characterized by excitation and/or depression. Restlessness, anxiety, dizziness, tinnitus, blurred vision, or tremors may occur, possibly proceeding to convulsions. However, excitement may be transient or absent, with depression being the first manifestation of an adverse reaction. This may quickly be followed by drowsiness merging into unconsciousness and respiratory arrest. Other central nervous system effects may be nausea, vomiting, chills, and constriction of the pupils.

The incidence of convulsions associated with the use of local anesthetics varies with the procedure used and the total dose administered. In a survey of studies of epidural anesthesia, overt toxicity progressing to convulsions occurred in approximately 0.1% of local anesthetic administrations.

Cardiovascular System Reactions: High doses or unintentional intravascular injection may lead to high plasma levels and related depression of the myocardium, decreased cardiac output, heartblock, hypotension, bradycardia, ventricular arrhythmias, including ventricular tachycardia and ventricular fibrillation, and cardiac arrest (See WARNINGS, PRECAUTIONS, and OVERDOSAGE).

Allergic: Allergic-type reactions are rare and may occur as a result of sensitivity to the local anesthetic or to other formulation ingredients, such as the antimicrobial preservative methylparaben contained in multiple-dose vials . These reactions are characterized by signs such as urticaria, pruritus, erythema, angioneurotic edema (including laryngeal edema), tachycardia, sneezing, nausea, vomiting, dizziness, syncope, excessive sweating, elevated temperature, and possibly, anaphylactoid-like symptomatology (including severe hypotension). Cross sensitivity among members of the amide-type local anesthetic group has been reported. The usefulness of screening for sensitivity has not been definitely established.

Neurologic: The incidences of adverse neurologic reactions associated with the use of local anesthetics may be related to the total dose of local anesthetic administered and are also dependent upon the particular drug used, the route of administration, and the physical status of the patient. Many of these effects may be related to local anesthetic techniques, with or without a contribution from the drug.

In the practice of caudal or lumbar epidural block, occasional unintentional penetration of the subarachnoid space by the catheter or needle may occur. Subsequent adverse effects may depend partially on the amount of drug administered intrathecally and the physiological and physical effects of a dural puncture. A high spinal is characterized by paralysis of the legs, loss of consciousness, respiratory paralysis, and bradycardia.

Neurologic effects following epidural or caudal anesthesia may include spinal block of varying magnitude (including high or total spinal block); hypotension secondary to spinal block; urinary retention; fecal and urinary incontinence; loss of perineal sensation and sexual function; persistent anesthesia, paresthesia, weakness, paralysis of the lower extremities and loss of sphincter control all of which may have slow, incomplete, or no recovery; headache; backache; septic meningitis; meningismus; slowing of labor; increased incidence of forceps delivery; and cranial nerve palsies due to traction on nerves from loss of cerebrospinal fluid.

Neurologic effects following other procedures or routes of administration may include persistent anesthesia, paresthesia, weakness, paralysis, all of which may have slow, incomplete, or no recovery.

OVERDOSAGE

Acute emergencies from local anesthetics are generally related to high plasma levels encountered during therapeutic use of local anesthetics or to unintended subarachnoid injection of local anesthetic solution (See ADVERSE REACTIONS, WARNINGS, and PRECAUTIONS).

Management of Local Anesthetic Emergencies: The first consideration is prevention, best accomplished by careful and constant monitoring of cardiovascular and respiratory vital signs and the patient's state of consciousness after each local anesthetic injection. At the first sign of change, oxygen should be administered.

The first step in the management of systemic toxic reactions, as well as underventilation or apnea due to unintentional subarachnoid injection of drug solution, consists of immediate attention to the establishment and maintenance of a patent airway and effective assisted or controlled ventilation with 100% oxygen with a delivery system capable of permitting immediate positive airway pressure by mask. This may prevent convulsions if they have not already occurred.

If necessary, use drugs to control the convulsions. A 50 mg to 100 mg bolus intravenous injection of succinylcholine will paralyze the patient without depressing the central nervous or cardiovascular systems and facilitate ventilation. A bolus intravenous dose of 5 mg to 10 mg of diazepam or 50 mg to 100 mg of thiopental will permit ventilation and counteract central nervous system stimulation, but these drugs also depress central nervous system, respiratory, and cardiac function, add to postictal depression and may result in apnea. Intravenous barbiturates, anticonvulsant agents, or muscle relaxants should only be administered by those familiar with their use. Immediately after the institution of these ventilatory measures, the adequacy of the circulation should be evaluated.

Endotracheal intubation, employing drugs and techniques familiar to the clinician, may be indicated after initial administration of oxygen by mask if difficulty is encountered in the maintenance of a patent airway, or if prolonged ventilatory support (assisted or controlled) is indicated.

Recent clinical data from patients experiencing local anesthetic-induced convulsions demonstrated rapid development of hypoxia, hypercarbia, and acidosis with bupivacaine within a minute of the onset of convulsions. These observations suggest that oxygen consumption and carbon dioxide production are greatly increased during local anesthetic convulsions and emphasize the importance of immediate and effective ventilation with oxygen which may avoid cardiac arrest.

If not treated immediately, convulsions with simultaneous hypoxia, hypercarbia, and acidosis plus myocardial depression from the direct effects of the local anesthetic may result in cardiac arrhythmias, bradycardia, asystole, ventricular fibrillation, or cardiac arrest. Respiratory abnormalities, including apnea, may occur. Underventilation or apnea due to unintentional subarachnoid injection of local anesthetic solution may produce these same signs and also lead to cardiac arrest if ventilatory support is not instituted. If cardiac arrest should occur, successful outcome may require prolonged resuscitative efforts.

The supine position is dangerous in pregnant women at term because of aortocaval compression by the gravid uterus. Therefore during treatment of systemic toxicity, maternal hypotension or fetal bradycardia following regional block, the parturient should be maintained in the left lateral decubitus position if possible, or manual displacement of the uterus off the great vessels be accomplished.

The mean seizure dosage of bupivacaine in rhesus monkeys was found to be 4.4 mg/kg with mean arterial plasma concentration of 4.5 mcg/mL. The intravenous and subcutaneous LD50 in mice is 6 mg/kg to 8 mg/kg and 38 mg/kg to 54 mg/kg respectively.

DOSAGE AND ADMINISTRATION

The dose of any local anesthetic administered varies with the anesthetic procedure, the area to be anesthetized, the vascularity of the tissues, the number of neuronal segments to be blocked, the depth of anesthesia and degree of muscle relaxation required, the duration of anesthesia desired, individual tolerance, and the physical condition of the patient. The smallest dose and concentration required to produce the desired result should be administered. Dosages of MARCAINE should be reduced for elderly and/or debilitated patients and patients with cardiac and/or liver disease. The rapid injection of a large volume of local anesthetic solution should be avoided and fractional (incremental) doses should be used when feasible.

For specific techniques and procedures, refer to standard textbooks.

There have been adverse event reports of chondrolysis in patients receiving intra-articular infusions of local anesthetics following arthroscopic and other surgical procedures. MARCAINE is not approved for this use (see WARNINGS and DOSAGE AND ADMINISTRATION).

In recommended doses, MARCAINE produces complete sensory block, but the effect on motor function differs among the three concentrations.

0.25%when used for caudal, epidural, or peripheral nerve block, produces incomplete motor block. Should be used for operations in which muscle relaxation is not important, or when another means of providing muscle relaxation is used concurrently. Onset of action may be slower than with the 0.5% or 0.75% solutions.

0.5% provides motor blockade for caudal, epidural, or nerve block, but muscle relaxation may be inadequate for operations in which complete muscle relaxation is essential.

0.75%produces complete motor block. Most useful for epidural block in abdominal operations requiring complete muscle relaxation, and for retrobulbar anesthesia. Not for obstetrical anesthesia.

The duration of anesthesia with MARCAINE is such that for most indications, a single dose is sufficient.

Maximum dosage limit must be individualized in each case after evaluating the size and physical status of the patient, as well as the usual rate of systemic absorption from a particular injection site.Most experience to date is with single doses of MARCAINE up to 175 mg without epinephrine; more or less drug may be used depending on individualization of each case.

These doses may be repeated up to once every three hours. In clinical studies to date, total daily doses have been up to 400 mg. Until further experience is gained, this dose should not be exceeded in 24 hours.

The dosages in Table 1 have generally proved satisfactory and are recommended as a guide for use in the average adult. These dosages should be reduced for elderly or debilitated patients. Until further experience is gained, MARCAINE is not recommended for pediatric patients younger than 12 years. MARCAINE is contraindicated for obstetrical paracervical blocks, and is not recommended for intravenous regional anesthesia (Bier Block).

Use in Epidural Anesthesia: During epidural administration of MARCAINE, 0.5% and 0.75% solutions should be administered in incremental doses of 3 mL to 5 mL with sufficient time between doses to detect toxic manifestations of unintentional intravascular or intrathecal injection. In obstetrics, only the 0.5% and 0.25% concentrations should be used; incremental doses of 3 mL to 5 mL of the 0.5% solution not exceeding 50 mg to 100 mg at any dosing interval are recommended.Use only the single-dose ampuls and single-dose vials for caudal or epidural anesthesia.

Unused portions of solution not containing preservatives, i.e., those supplied in single-dose ampuls and single-dose vials, should be discarded following initial use.

This product should be inspected visually for particulate matter and discoloration prior to administration whenever solution and container permit. Solutions which are discolored or which contain particulate matter should not be administered.

Table 1. Recommended Concentrations and Doses of MARCAINE
Type of Block | Conc. | Each Dose; (mL) (mg) |  | Motor Block^1
Local; infiltration | 0.25%^4 | up to max. | up to max. | _
Epidural | 0.75%^2,4 | 10-20 | 75-150 | complete
Epidural | 0.5%^4 | 10-20 | 50-100 | moderate to complete
Epidural | 0.25%^4 | 10-20 | 25-50 | partial to moderate
Caudal | 0.5%^4 | 15-30 | 75-150 | moderate to complete
Caudal | 0.25%^4 | 15-30 | 37.5-75 | moderate
Peripheral nerves | 0.5%^4 | 5 to max. | 25 to max. | moderate to complete
Peripheral nerves | 0.25%^4 | 5 to max. | 12.5 to max. | moderate to complete
Retrobulbar^3 | 0.75%^4 | 2-4 | 15-30 | complete
Sympathetic | 0.25% | 20-50 | 50-125 | _

^1 With continuous (intermittent) techniques, repeat doses increase the degree of motor block. The first repeat dose of 0.5% may produce complete motor block. Intercostal nerve block with 0.25% may also produce complete motor block for intra-abdominal surgery.
^2 For single-dose use, not for intermittent epidural technique. Not for obstetrical anesthesia.
^3 See PRECAUTIONS.
^4 Solutions with or without epinephrine.

HOW SUPPLIED

These solutions are not for spinal anesthesia.

Store at 20 to 25°C (68 to 77°F). [See USP Controlled Room Temperature.]

MARCAINE―Solutions of MARCAINE that do not contain epinephrine may be autoclaved. Autoclave at 15-pound pressure, 121°C (250°F) for 15 minutes.

Unit of Sale | Concentration | Each
0.5% Contains 5 mg bupivacaine hydrochloride per mL.
NDC 0409-1560-10; Tray of 10 | 50 mg/10 mL; (5 mg/mL) | NDC 0409-1560-18; Single-dose vial

Hospira, Inc., Lake Forest, IL 60045 USA

LAB-1178-1.0

Revised: 11/2017

KENALOG®-40 INJECTION (triamcinolone acetonide injectable suspension, USP)

NOT FOR USE IN NEONATES
CONTAINS BENZYL ALCOHOL

For Intramuscular or Intra-articular Use Only
NOT FOR INTRAVENOUS, INTRADERMAL, INTRAOCULAR, EPIDURAL, OR INTRATHECAL USE

DESCRIPTION

Kenalog®-40 Injection (triamcinolone acetonide injectable suspension, USP) is a synthetic glucocorticoid corticosteroid with anti-inflammatory action. THIS FORMULATION IS SUITABLE FOR INTRAMUSCULAR AND INTRA-ARTICULAR USE ONLY. THIS FORMULATION IS NOT FOR INTRADERMAL INJECTION.

Each mL of the sterile aqueous suspension provides 40 mg triamcinolone acetonide, with 0.66% sodium chloride for isotonicity, 0.99% (w/v) benzyl alcohol as a preservative, 0.63% carboxymethylcellulose sodium, and 0.04% polysorbate 80. Sodium hydroxide or hydrochloric acid may be present to adjust pH to 5.0 to 7.5. At the time of manufacture, the air in the container is replaced by nitrogen.

The chemical name for triamcinolone acetonide is 9-Fluoro-11β,16α,17,21-tetrahydroxypregna-1,4-diene-3,20-dione cyclic 16,17-acetal with acetone. Its structural formula is:

Triamcinolone acetonide occurs as a white to cream-colored, crystalline powder having not more than a slight odor and is practically insoluble in water and very soluble in alcohol.

CLINICAL PHARMACOLOGY

Glucocorticoids, naturally occurring and synthetic, are adrenocortical steroids that are readily absorbed from the gastrointestinal tract.

Naturally occurring glucocorticoids (hydrocortisone and cortisone), which also have salt-retaining properties, are used as replacement therapy in adrenocortical deficiency states. Synthetic analogs such as triamcinolone are primarily used for their anti-inflammatory effects in disorders of many organ systems.

Kenalog-40 Injection has an extended duration of effect which may be sustained over a period of several weeks. Studies indicate that following a single intramuscular dose of 60 mg to 100 mg of triamcinolone acetonide, adrenal suppression occurs within 24 to 48 hours and then gradually returns to normal, usually in 30 to 40 days. This finding correlates closely with the extended duration of therapeutic action achieved with the drug.

INDICATIONS AND USAGE

Intramuscular

Where oral therapy is not feasible, injectable corticosteroid therapy, including Kenalog-40 Injection (triamcinolone acetonide injectable suspension, USP) is indicated for intramuscular use as follows:

Allergic states: Control of severe or incapacitating allergic conditions intractable to adequate trials of conventional treatment in asthma, atopic dermatitis, contact dermatitis, drug hypersensitivity reactions, perennial or seasonal allergic rhinitis, serum sickness, transfusion reactions.

Dermatologic diseases: Bullous dermatitis herpetiformis, exfoliative erythroderma, mycosis fungoides, pemphigus, severe erythema multiforme (Stevens-Johnson syndrome).

Endocrine disorders: Primary or secondary adrenocortical insufficiency (hydrocortisone or cortisone is the drug of choice; synthetic analogs may be used in conjunction with mineralocorticoids where applicable; in infancy, mineralocorticoid supplementation is of particular importance), congenital adrenal hyperplasia, hypercalcemia associated with cancer, nonsuppurative thyroiditis.

Gastrointestinal diseases: To tide the patient over a critical period of the disease in regional enteritis and ulcerative colitis.

Hematologic disorders: Acquired (autoimmune) hemolytic anemia, Diamond-Blackfan anemia, pure red cell aplasia, selected cases of secondary thrombocytopenia.

Miscellaneous: Trichinosis with neurologic or myocardial involvement, tuberculous meningitis with subarachnoid block or impending block when used with appropriate antituberculous chemotherapy.

Neoplastic diseases: For the palliative management of leukemias and lymphomas.

Nervous system: Acute exacerbations of multiple sclerosis; cerebral edema associated with primary or metastatic brain tumor or craniotomy.

Ophthalmic diseases: Sympathetic ophthalmia, temporal arteritis, uveitis, and ocular inflammatory conditions unresponsive to topical corticosteroids.

Renal diseases: To induce diuresis or remission of proteinuria in idiopathic nephrotic syndrome or that due to lupus erythematosus.

Respiratory diseases: Berylliosis, fulminating or disseminated pulmonary tuberculosis when used concurrently with appropriate antituberculous chemotherapy, idiopathic eosinophilic pneumonias, symptomatic sarcoidosis.

Rheumatic disorders: As adjunctive therapy for short-term administration (to tide the patient over an acute episode or exacerbation) in acute gouty arthritis; acute rheumatic carditis; ankylosing spondylitis; psoriatic arthritis; rheumatoid arthritis, including juvenile rheumatoid arthritis (selected cases may require low-dose maintenance therapy). For the treatment of dermatomyositis, polymyositis, and systemic lupus erythematosus.

Intra-Articular

The intra-articular or soft tissue administration of Kenalog-40 Injection is indicated as adjunctive therapy for short-term administration (to tide the patient over an acute episode or exacerbation) in acute gouty arthritis, acute and subacute bursitis, acute nonspecific tenosynovitis, epicondylitis, rheumatoid arthritis, synovitis, or osteoarthritis.

CONTRAINDICATIONS

Kenalog-40 Injection is contraindicated in patients who are hypersensitive to any components of this product (see WARNINGS: General).

Intramuscular corticosteroid preparations are contraindicated for idiopathic thrombocytopenic purpura.

WARNINGS

Serious Neurologic Adverse Reactions with Epidural Administration

Serious neurologic events, some resulting in death, have been reported with epidural injection of corticosteroids (see WARNINGS: Neurologic). Specific events reported include, but are not limited to, spinal cord infarction, paraplegia, quadriplegia, cortical blindness, and stroke. These serious neurologic events have been reported with and without use of fluoroscopy. The safety and effectiveness of epidural administration of corticosteroids have not been established, and corticosteroids are not approved for this use.

General

Exposure to excessive amounts of benzyl alcohol has been associated with toxicity (hypotension, metabolic acidosis), particularly in neonates, and an increased incidence of kernicterus, particularly in small preterm infants. There have been rare reports of deaths, primarily in preterm infants, associated with exposure to excessive amounts of benzyl alcohol. The amount of benzyl alcohol from medications is usually considered negligible compared to that received in flush solutions containing benzyl alcohol. Administration of high dosages of medications containing this preservative must take into account the total amount of benzyl alcohol administered. The amount of benzyl alcohol at which toxicity may occur is not known. If the patient requires more than the recommended dosages or other medications containing this preservative, the practitioner must consider the daily metabolic load of benzyl alcohol from these combined sources (see PRECAUTIONS: Pediatric Use).

Rare instances of anaphylaxis have occurred in patients receiving corticosteroid therapy (see ADVERSE REACTIONS). Cases of serious anaphylaxis, including death, have been reported in individuals receiving triamcinolone acetonide injection, regardless of the route of administration.

Because Kenalog-40 Injection (triamcinolone acetonide injectable suspension, USP) is a suspension, it should not be administered intravenously.

Unless a deep intramuscular injection is given, local atrophy is likely to occur. (For recommendations on injection techniques, see DOSAGE AND ADMINISTRATION.) Due to the significantly higher incidence of local atrophy when the material is injected into the deltoid area, this injection site should be avoided in favor of the gluteal area.

Increased dosage of rapidly acting corticosteroids is indicated in patients on corticosteroid therapy subjected to any unusual stress before, during, and after the stressful situation. Kenalog-40 Injection is a long-acting preparation, and is not suitable for use in acute stress situations. To avoid drug-induced adrenal insufficiency, supportive dosage may be required in times of stress (such as trauma, surgery, or severe illness) both during treatment with Kenalog-40 Injection and for a year afterwards.

Results from one multicenter, randomized, placebo-controlled study with methylprednisolone hemisuccinate, an intravenous corticosteroid, showed an increase in early (at 2 weeks) and late (at 6 months) mortality in patients with cranial trauma who were determined not to have other clear indications for corticosteroid treatment. High doses of systemic corticosteroids, including Kenalog-40 Injection, should not be used for the treatment of traumatic brain injury.

Cardio-Renal

Average and large doses of corticosteroids can cause elevation of blood pressure, salt and water retention, and increased excretion of potassium. These effects are less likely to occur with the synthetic derivatives except when they are used in large doses. Dietary salt restriction and potassium supplementation may be necessary (see PRECAUTIONS). All corticosteroids increase calcium excretion.

Literature reports suggest an apparent association between use of corticosteroids and left ventricular free wall rupture after a recent myocardial infarction; therefore, therapy with corticosteroids should be used with great caution in these patients.

Endocrine

Corticosteroids can produce reversible hypothalamic-pituitary-adrenal (HPA) axis suppression with the potential for glucocorticosteroid insufficiency after withdrawal of treatment.

Metabolic clearance of corticosteroids is decreased in hypothyroid patients and increased in hyperthyroid patients. Changes in thyroid status of the patient may necessitate adjustment in dosage.

Infections

General

Patients who are on corticosteroids are more susceptible to infections than are healthy individuals. There may be decreased resistance and inability to localize infection when corticosteroids are used. Infection with any pathogen (viral, bacterial, fungal, protozoan, or helminthic) in any location of the body may be associated with the use of corticosteroids alone or in combination with other immunosuppressive agents. These infections may be mild to severe. With increasing doses of corticosteroids, the rate of occurrence of infectious complications increases. Corticosteroids may also mask some signs of current infection.

Fungal Infections

Corticosteroids may exacerbate systemic fungal infections and therefore should not be used in the presence of such infections unless they are needed to control drug reactions. There have been cases reported in which concomitant use of amphotericin B and hydrocortisone was followed by cardiac enlargement and congestive heart failure (see PRECAUTIONS: Drug Interactions: Amphotericin B injection and potassium-depleting agents).

Special Pathogens

Latent disease may be activated or there may be an exacerbation of intercurrent infections due to pathogens, including those caused by Amoeba, Candida, Cryptococcus, Mycobacterium, Nocardia, Pneumocystis, or Toxoplasma.

It is recommended that latent amebiasis or active amebiasis be ruled out before initiating corticosteroid therapy in any patient who has spent time in the tropics or in any patient with unexplained diarrhea.

Similarly, corticosteroids should be used with great care in patients with known or suspected Strongyloides (threadworm) infestation. In such patients, corticosteroid-induced immunosuppression may lead to Strongyloides hyperinfection and dissemination with widespread larval migration, often accompanied by severe enterocolitis and potentially fatal gram-negative septicemia.

Corticosteroids should not be used in cerebral malaria.

Tuberculosis

The use of corticosteroids in patients with active tuberculosis should be restricted to those cases of fulminating or disseminated tuberculosis in which the corticosteroid is used for the management of the disease in conjunction with an appropriate anti-tuberculosis regimen. If corticosteroids are indicated in patients with latent tuberculosis or tuberculin reactivity, close observation is necessary as reactivation of the disease may occur. During prolonged corticosteroid therapy, these patients should receive chemoprophylaxis.

Vaccination

Administration of live or live, attenuated vaccines is contraindicated in patients receiving immunosuppressive doses of corticosteroids. Killed or inactivated vaccines may be administered. However, the response to such vaccines cannot be predicted. Immunization procedures may be undertaken in patients who are receiving corticosteroids as replacement therapy, e.g, for Addison’s disease.

Viral Infections

Chicken pox and measles can have a more serious or even fatal course in pediatric and adult patients on corticosteroids. In pediatric and adult patients who have not had these diseases, particular care should be taken to avoid exposure. The contribution of the underlying disease and/or prior corticosteroid treatment to the risk is also not known. If exposed to chicken pox, prophylaxis with varicella zoster immune globulin (VZIG) may be indicated. If exposed to measles, prophylaxis with immunoglobulin (IG) may be indicated. (See the respective package inserts for complete VZIG and IG prescribing information.) If chicken pox develops, treatment with antiviral agents should be considered.

Neurologic

Epidural and intrathecal administration of this product is not recommended. Reports of serious medical events, including death, have been associated with epidural and intrathecal routes of corticosteroid administration (see ADVERSE REACTIONS: Gastrointestinal and Neurologic/Psychiatric).

Ophthalmic

Use of corticosteroids may produce posterior subcapsular cataracts, glaucoma with possible damage to the optic nerves, and may enhance the establishment of secondary ocular infections due to bacteria, fungi, or viruses. The use of oral corticosteroids is not recommended in the treatment of optic neuritis and may lead to an increase in the risk of new episodes. Corticosteroids should not be used in active ocular herpes simplex.

Adequate studies to demonstrate the safety of Kenalog Injection use by intraturbinal, subconjunctival, sub-Tenons, retrobulbar, and intraocular (intravitreal) injections have not been performed. Endophthalmitis, eye inflammation, increased intraocular pressure, and visual disturbances including vision loss have been reported with intravitreal administration. Administration of Kenalog Injection intraocularly or into the nasal turbinates is not recommended.

Intraocular injection of corticosteroid formulations containing benzyl alcohol, such as Kenalog Injection, is not recommended because of potential toxicity from the benzyl alcohol.

PRECAUTIONS

General

This product, like many other steroid formulations, is sensitive to heat. Therefore, it should not be autoclaved when it is desirable to sterilize the exterior of the vial.

The lowest possible dose of corticosteroid should be used to control the condition under treatment. When reduction in dosage is possible, the reduction should be gradual.

Since complications of treatment with glucocorticoids are dependent on the size of the dose and the duration of treatment, a risk/benefit decision must be made in each individual case as to dose and duration of treatment and as to whether daily or intermittent therapy should be used.

Kaposi’s sarcoma has been reported to occur in patients receiving corticosteroid therapy, most often for chronic conditions. Discontinuation of corticosteroids may result in clinical improvement.

Cardio-Renal

As sodium retention with resultant edema and potassium loss may occur in patients receiving corticosteroids, these agents should be used with caution in patients with congestive heart failure, hypertension, or renal insufficiency.

Endocrine

Drug-induced secondary adrenocortical insufficiency may be minimized by gradual reduction of dosage. This type of relative insufficiency may persist for months after discontinuation of therapy; therefore, in any situation of stress occurring during that period, hormone therapy should be reinstituted. Since mineralocorticoid secretion may be impaired, salt and/or a mineralocorticoid should be administered concurrently.

Gastrointestinal

Steroids should be used with caution in active or latent peptic ulcers, diverticulitis, fresh intestinal anastomoses, and nonspecific ulcerative colitis, since they may increase the risk of a perforation.

Signs of peritoneal irritation following gastrointestinal perforation in patients receiving corticosteroids may be minimal or absent.

There is an enhanced effect of corticosteroids in patients with cirrhosis.

Intra-Articular and Soft Tissue Administration

Intra-articularly injected corticosteroids may be systemically absorbed.

Appropriate examination of any joint fluid present is necessary to exclude a septic process.

A marked increase in pain accompanied by local swelling, further restriction of joint motion, fever, and malaise are suggestive of septic arthritis. If this complication occurs and the diagnosis of sepsis is confirmed, appropriate antimicrobial therapy should be instituted.

Injection of a steroid into an infected site is to be avoided. Local injection of a steroid into a previously infected joint is not usually recommended.

Corticosteroid injection into unstable joints is generally not recommended.

Intra-articular injection may result in damage to joint tissues (see ADVERSE REACTIONS: Musculoskeletal).

Musculoskeletal

Corticosteroids decrease bone formation and increase bone resorption both through their effect on calcium regulation (i.e, decreasing absorption and increasing excretion) and inhibition of osteoblast function. This, together with a decrease in the protein matrix of the bone secondary to an increase in protein catabolism, and reduced sex hormone production, may lead to inhibition of bone growth in pediatric patients and the development of osteoporosis at any age. Special consideration should be given to patients at increased risk of osteoporosis (ie, postmenopausal women) before initiating corticosteroid therapy.

Neuro-Psychiatric

Although controlled clinical trials have shown corticosteroids to be effective in speeding the resolution of acute exacerbations of multiple sclerosis, they do not show that they affect the ultimate outcome or natural history of the disease. The studies do show that relatively high doses of corticosteroids are necessary to demonstrate a significant effect. (See DOSAGE AND ADMINISTRATION.)

An acute myopathy has been observed with the use of high doses of corticosteroids, most often occurring in patients with disorders of neuromuscular transmission (eg, myasthenia gravis), or in patients receiving concomitant therapy with neuromuscular blocking drugs (eg, pancuronium). This acute myopathy is generalized, may involve ocular and respiratory muscles, and may result in quadriparesis. Elevation of creatinine kinase may occur. Clinical improvement or recovery after stopping corticosteroids may require weeks to years.

Psychiatric derangements may appear when corticosteroids are used, ranging from euphoria, insomnia, mood swings, personality changes, and severe depression to frank psychotic manifestations. Also, existing emotional instability or psychotic tendencies may be aggravated by corticosteroids.

Ophthalmic

Intraocular pressure may become elevated in some individuals. If steroid therapy is continued for more than 6 weeks, intraocular pressure should be monitored.

Information for Patients

Patients should be warned not to discontinue the use of corticosteroids abruptly or without medical supervision, to advise any medical attendants that they are taking corticosteroids, and to seek medical advice at once should they develop fever or other signs of infection.

Persons who are on corticosteroids should be warned to avoid exposure to chicken pox or measles. Patients should also be advised that if they are exposed, medical advice should be sought without delay.

Drug Interactions

Aminoglutethimide: Aminoglutethimide may lead to a loss of corticosteroid-induced adrenal suppression.

Amphotericin B injection and potassium-depleting agents: When corticosteroids are administered concomitantly with potassium-depleting agents (ie, amphotericin B, diuretics), patients should be observed closely for development of hypokalemia. There have been cases reported in which concomitant use of amphotericin B and hydrocortisone was followed by cardiac enlargement and congestive heart failure.

Antibiotics: Macrolide antibiotics have been reported to cause a significant decrease in corticosteroid clearance.

Anticholinesterases: Concomitant use of anticholinesterase agents and corticosteroids may produce severe weakness in patients with myasthenia gravis. If possible, anticholinesterase agents should be withdrawn at least 24 hours before initiating corticosteroid therapy.

Anticoagulants, oral: Coadministration of corticosteroids and warfarin usually results in inhibition of response to warfarin, although there have been some conflicting reports. Therefore, coagulation indices should be monitored frequently to maintain the desired anticoagulant effect.

Antidiabetics: Because corticosteroids may increase blood glucose concentrations, dosage adjustments of antidiabetic agents may be required.

Antitubercular drugs: Serum concentrations of isoniazid may be decreased.

Cholestyramine: Cholestyramine may increase the clearance of corticosteroids.

Cyclosporine: Increased activity of both cyclosporine and corticosteroids may occur when the two are used concurrently. Convulsions have been reported with this concurrent use.

Digitalis glycosides: Patients on digitalis glycosides may be at increased risk of arrhythmias due to hypokalemia.

Estrogens, including oral contraceptives: Estrogens may decrease the hepatic metabolism of certain corticosteroids, thereby increasing their effect.

Hepatic enzyme inducers (eg, barbiturates, phenytoin, carbamazepine, rifampin): Drugs which induce hepatic microsomal drug metabolizing enzyme activity may enhance the metabolism of corticosteroids and require that the dosage of the corticosteroid be increased.

Ketoconazole: Ketoconazole has been reported to decrease the metabolism of certain corticosteroids by up to 60%, leading to an increased risk of corticosteroid side effects.

Nonsteroidal anti-inflammatory drugs (NSAIDs): Concomitant use of aspirin (or other nonsteroidal anti-inflammatory drugs) and corticosteroids increases the risk of gastrointestinal side effects. Aspirin should be used cautiously in conjunction with corticosteroids in hypoprothrombinemia. The clearance of salicylates may be increased with concurrent use of corticosteroids.

Skin tests: Corticosteroids may suppress reactions to skin tests.

Vaccines: Patients on prolonged corticosteroid therapy may exhibit a diminished response to toxoids and live or inactivated vaccines due to inhibition of antibody response. Corticosteroids may also potentiate the replication of some organisms contained in live attenuated vaccines. Routine administration of vaccines or toxoids should be deferred until corticosteroid therapy is discontinued if possible (see WARNINGS: Infections: Vaccination).

Carcinogenesis, Mutagenesis, Impairment of Fertility

No adequate studies have been conducted in animals to determine whether corticosteroids have a potential for carcinogenesis or mutagenesis.

Steroids may increase or decrease motility and number of spermatozoa in some patients.

Pregnancy

Teratogenic Effects: Pregnancy Category C

Corticosteroids have been shown to be teratogenic in many species when given in doses equivalent to the human dose. Animal studies in which corticosteroids have been given to pregnant mice, rats, and rabbits have yielded an increased incidence of cleft palate in the offspring. There are no adequate and well-controlled studies in pregnant women. Corticosteroids should be used during pregnancy only if the potential benefit justifies the potential risk to the fetus. Infants born to mothers who have received corticosteroids during pregnancy should be carefully observed for signs of hypoadrenalism.

Nursing Mothers

Systemically administered corticosteroids appear in human milk and could suppress growth, interfere with endogenous corticosteroid production, or cause other untoward effects. Caution should be exercised when corticosteroids are administered to a nursing woman.

Pediatric Use

This product contains benzyl alcohol as a preservative. Benzyl alcohol, a component of this product, has been associated with serious adverse events and death, particularly in pediatric patients. The “gasping syndrome” (characterized by central nervous system depression, metabolic acidosis, gasping respirations, and high levels of benzyl alcohol and its metabolites found in the blood and urine) has been associated with benzyl alcohol dosages >99 mg/kg/day in neonates and low-birth-weight neonates. Additional symptoms may include gradual neurological deterioration, seizures, intracranial hemorrhage, hematologic abnormalities, skin breakdown, hepatic and renal failure, hypotension, bradycardia, and cardiovascular collapse. Although normal therapeutic doses of this product deliver amounts of benzyl alcohol that are substantially lower than those reported in association with the “gasping syndrome,” the minimum amount of benzyl alcohol at which toxicity may occur is not known. Premature and low-birth-weight infants, as well as patients receiving high dosages, may be more likely to develop toxicity. Practitioners administering this and other medications containing benzyl alcohol should consider the combined daily metabolic load of benzyl alcohol from all sources.

The efficacy and safety of corticosteroids in the pediatric population are based on the well-established course of effect of corticosteroids which is similar in pediatric and adult populations. Published studies provide evidence of efficacy and safety in pediatric patients for the treatment of nephrotic syndrome (>2 years of age), and aggressive lymphomas and leukemias (>1 month of age). Other indications for pediatric use of corticosteroids, eg, severe asthma and wheezing, are based on adequate and well-controlled trials conducted in adults, on the premises that the course of the diseases and their pathophysiology are considered to be substantially similar in both populations.

The adverse effects of corticosteroids in pediatric patients are similar to those in adults (see ADVERSE REACTIONS). Like adults, pediatric patients should be carefully observed with frequent measurements of blood pressure, weight, height, intraocular pressure, and clinical evaluation for the presence of infection, psychosocial disturbances, thromboembolism, peptic ulcers, cataracts, and osteoporosis. Pediatric patients who are treated with corticosteroids by any route, including systemically administered corticosteroids, may experience a decrease in their growth velocity. This negative impact of corticosteroids on growth has been observed at low systemic doses and in the absence of laboratory evidence of HPA axis suppression (ie, cosyntropin stimulation and basal cortisol plasma levels). Growth velocity may therefore be a more sensitive indicator of systemic corticosteroid exposure in pediatric patients than some commonly used tests of HPA axis function. The linear growth of pediatric patients treated with corticosteroids should be monitored, and the potential growth effects of prolonged treatment should be weighed against clinical benefits obtained and the availability of treatment alternatives. In order to minimize the potential growth effects of corticosteroids, pediatric patients should be titrated to the lowest effective dose.

Geriatric Use

No overall differences in safety or effectiveness were observed between elderly subjects and younger subjects, and other reported clinical experience has not identified differences in responses between the elderly and younger patients, but greater sensitivity of some older individuals cannot be ruled out.

ADVERSE REACTIONS

(listed alphabetically under each subsection)

The following adverse reactions may be associated with corticosteroid therapy:

Allergic reactions: Anaphylaxis including death, angioedema.

Cardiovascular: Bradycardia, cardiac arrest, cardiac arrhythmias, cardiac enlargement, circulatory collapse, congestive heart failure, fat embolism, hypertension, hypertrophic cardiomyopathy in premature infants, myocardial rupture following recent myocardial infarction (see WARNINGS), pulmonary edema, syncope, tachycardia, thromboembolism, thrombophlebitis, vasculitis.

Dermatologic: Acne, allergic dermatitis, cutaneous and subcutaneous atrophy, dry scaly skin, ecchymoses and petechiae, edema, erythema, hyperpigmentation, hypopigmentation, impaired wound healing, increased sweating, lupus erythematosus-like lesions, purpura, rash, sterile abscess, striae, suppressed reactions to skin tests, thin fragile skin, thinning scalp hair, urticaria.

Endocrine: Decreased carbohydrate and glucose tolerance, development of cushingoid state, glycosuria, hirsutism, hypertrichosis, increased requirements for insulin or oral hypoglycemic agents in diabetes, manifestations of latent diabetes mellitus, menstrual irregularities, secondary adrenocortical and pituitary unresponsiveness (particularly in times of stress, as in trauma, surgery, or illness), suppression of growth in pediatric patients.

Fluid and electrolyte disturbances: Congestive heart failure in susceptible patients, fluid retention, hypokalemic alkalosis, potassium loss, sodium retention.

Gastrointestinal: Abdominal distention, bowel/bladder dysfunction (after intrathecal administration [see WARNINGS: Neurologic]), elevation in serum liver enzyme levels (usually reversible upon discontinuation), hepatomegaly, increased appetite, nausea, pancreatitis, peptic ulcer with possible perforation and hemorrhage, perforation of the small and large intestine (particularly in patients with inflammatory bowel disease), ulcerative esophagitis.

Metabolic: Negative nitrogen balance due to protein catabolism.

Musculoskeletal: Aseptic necrosis of femoral and humeral heads, calcinosis (following intra-articular or intralesional use), Charcot-like arthropathy, loss of muscle mass, muscle weakness, osteoporosis, pathologic fracture of long bones, post injection flare (following intra-articular use), steroid myopathy, tendon rupture, vertebral compression fractures.

Neurologic/Psychiatric: Convulsions, depression, emotional instability, euphoria, headache, increased intracranial pressure with papilledema (pseudotumor cerebri) usually following discontinuation of treatment, insomnia, mood swings, neuritis, neuropathy, paresthesia, personality changes, psychiatric disorders, vertigo. Arachnoiditis, meningitis, paraparesis/paraplegia, and sensory disturbances have occurred after intrathecal administration. Spinal cord infarction, paraplegia, quadriplegia, cortical blindness, and stroke (including brainstem) have been reported after epidural administration of corticosteroids (see WARNINGS: Serious Neurologic Adverse Reactions with Epidural Administration and WARNINGS: Neurologic).

Ophthalmic: Exophthalmos, glaucoma, increased intraocular pressure, posterior subcapsular cataracts, rare instances of blindness associated with periocular injections.

Other: Abnormal fat deposits, decreased resistance to infection, hiccups, increased or decreased motility and number of spermatozoa, malaise, moon face, weight gain.

OVERDOSAGE

Treatment of acute overdosage is by supportive and symptomatic therapy. For chronic overdosage in the face of severe disease requiring continuous steroid therapy, the dosage of the corticosteroid may be reduced only temporarily, or alternate day treatment may be introduced.

DOSAGE AND ADMINISTRATION

General

NOTE: CONTAINS BENZYL ALCOHOL (see PRECAUTIONS).

The initial dose of Kenalog-40 Injection may vary from 2.5 mg to 100 mg per day depending on the specific disease entity being treated (see Dosage section below). However, in certain overwhelming, acute, life-threatening situations, administration in dosages exceeding the usual dosages may be justified and may be in multiples of the oral dosages.

IT SHOULD BE EMPHASIZED THAT DOSAGE REQUIREMENTS ARE VARIABLE AND MUST BE INDIVIDUALIZED ON THE BASIS OF THE DISEASE UNDER TREATMENT AND THE RESPONSE OF THE PATIENT. After a favorable response is noted, the proper maintenance dosage should be determined by decreasing the initial drug dosage in small decrements at appropriate time intervals until the lowest dosage which will maintain an adequate clinical response is reached. Situations which may make dosage adjustments necessary are changes in clinical status secondary to remissions or exacerbations in the disease process, the patient’s individual drug responsiveness, and the effect of patient exposure to stressful situations not directly related to the disease entity under treatment. In this latter situation it may be necessary to increase the dosage of the corticosteroid for a period of time consistent with the patient’s condition. If after long-term therapy the drug is to be stopped, it is recommended that it be withdrawn gradually rather than abruptly.

Dosage

SYSTEMIC

The suggested initial dose is 60 mg, injected deeply into the gluteal muscle. Atrophy of subcutaneous fat may occur if the injection is not properly given. Dosage is usually adjusted within the range of 40 mg to 80 mg, depending upon patient response and duration of relief. However, some patients may be well controlled on doses as low as 20 mg or less.

Hay fever or pollen asthma: Patients with hay fever or pollen asthma who are not responding to pollen administration and other conventional therapy may obtain a remission of symptoms lasting throughout the pollen season after a single injection of 40 mg to 100 mg.

In the treatment of acute exacerbations of multiple sclerosis, daily doses of 160 mg of triamcinolone for a week followed by 64 mg every other day for one month are recommended (see PRECAUTIONS: Neuro-Psychiatric).

In pediatric patients, the initial dose of triamcinolone may vary depending on the specific disease entity being treated. The range of initial doses is 0.11 to 1.6 mg/kg/day in 3 or 4 divided doses (3.2 to 48 mg/m2bsa/day).

For the purpose of comparison, the following is the equivalent milligram dosage of the various glucocorticoids:

Cortisone, 25 | Triamcinolone, 4
Hydrocortisone, 20 | Paramethasone, 2
Prednisolone, 5 | Betamethasone, 0.75
Prednisone, 5 | Dexamethasone, 0.75
Methylprednisolone, 4

These dose relationships apply only to oral or intravenous administration of these compounds. When these substances or their derivatives are injected intramuscularly or into joint spaces, their relative properties may be greatly altered.

LOCAL

Intra-articular administration: A single local injection of triamcinolone acetonide is frequently sufficient, but several injections may be needed for adequate relief of symptoms.

Initial dose: 2.5 mg to 5 mg for smaller joints and from 5 mg to 15 mg for larger joints, depending on the specific disease entity being treated. For adults, doses up to 10 mg for smaller areas and up to 40 mg for larger areas have usually been sufficient. Single injections into several joints, up to a total of 80 mg, have been given.

Administration

GENERAL

STRICT ASEPTIC TECHNIQUE IS MANDATORY. The vial should be shaken before use to ensure a uniform suspension. Prior to withdrawal, the suspension should be inspected for clumping or granular appearance (agglomeration). An agglomerated product results from exposure to freezing temperatures and should not be used. After withdrawal, Kenalog-40 Injection should be injected without delay to prevent settling in the syringe. Careful technique should be employed to avoid the possibility of entering a blood vessel or introducing infection.

SYSTEMIC

For systemic therapy, injection should be made deeply into the gluteal muscle (see WARNINGS). For adults, a minimum needle length of 1½ inches is recommended. In obese patients, a longer needle may be required. Use alternative sites for subsequent injections.

LOCAL

For treatment of joints, the usual intra-articular injection technique should be followed. If an excessive amount of synovial fluid is present in the joint, some, but not all, should be aspirated to aid in the relief of pain and to prevent undue dilution of the steroid.

With intra-articular administration, prior use of a local anesthetic may often be desirable. Care should be taken with this kind of injection, particularly in the deltoid region, to avoid injecting the suspension into the tissues surrounding the site, since this may lead to tissue atrophy.

In treating acute nonspecific tenosynovitis, care should be taken to ensure that the injection of the corticosteroid is made into the tendon sheath rather than the tendon substance. Epicondylitis may be treated by infiltrating the preparation into the area of greatest tenderness.

HOW SUPPLIED

Kenalog®-40 Injection (triamcinolone acetonide injectable suspension, USP) is supplied in vials providing 40 mg triamcinolone acetonide per mL.

40 mg/mL, 1 mL vial | NDC 0003-0293-05

Bristol-Myers Squibb Company
Princeton, NJ 08543 USA
Product of Spain 1221153A7

Revised: January 2016

Assembled and Distributed by IT3 Medical, LLC
190 E Stacy Rd, Ste 306-298, Allen, TX 75002

For questions or comments:
info@IT3-Medical.com, www.IT3-Medical.com

Storage

Store at controlled room temperature, 20°–25°C (68°–77°F), avoid freezing and protect from light. Do not refrigerate.

MCKESSON ALCOHOL PREP PAD- isopropyl alcohol swab

Drug Facts

Active ingredient

Isopropyl Alcohol 70% v/v

Purpose

First Aid Antiseptic

Use

For preparation of the skin prior to an injection

Warnings

- For external use only
- Flammable, keep away from fire or flame

- Do not use with electrocautery procedures
- Do not use in the eyes
- Do not apply to irritated skin

- Stop use if pain, irritation, redness, or swelling occurs, discontinue use and consult a physician.

KEEP OUT OF REACH OF CHILDREN

- Keep out from reach of children. If swallowed, get medical help or contact a Poison Control Center right away.

Directions

- Open packet
- Remove pad
- Apply topically as needed to cleanse intended area. Discard after single use.

Other information

- Store at room temperature 59-86°F (15-30°C)
- Contents sterile in unopened, undamaged package

Inactive ingredients

purified water

CORTAREN CORTICOSTEROID/ANTI-INFLAMMATORY SYSTEM

Contents:

1-1 mL Dexamethasone Sodium Phosphate (4 mg/mL)

1-10 mL Marcaine 0.5%

1- 1 mL Kenalog -40 (40mg/mL)

1-3mL Syringe w/ 18-22 Gauge 1- 1/2in Needle (Draw)

1-22-27 Gauge 1-1/2in Needle (Administer)

1-3x3 Gauze Sponge Sterile Square

1- Bandage 1 x 3in

4- Alcohol Prep Pads